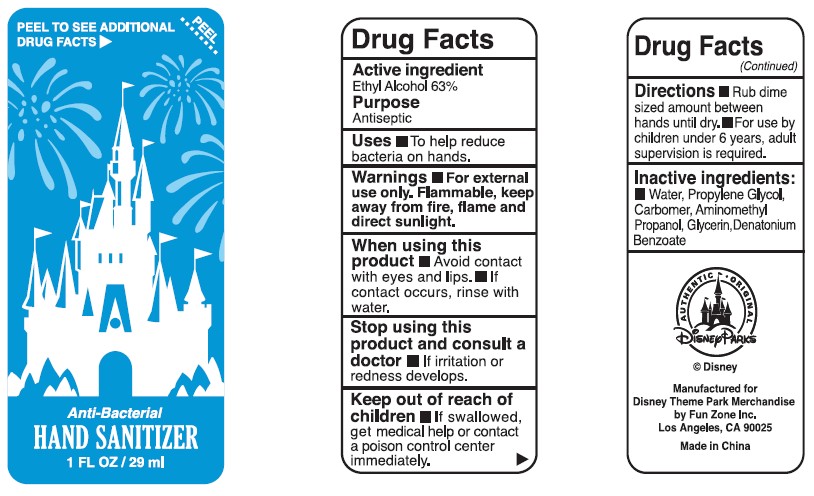 DRUG LABEL: Anti-Bacterial Hand Sanitizer
NDC: 69583-003 | Form: GEL
Manufacturer: Fun Zone, Inc.
Category: otc | Type: HUMAN OTC DRUG LABEL
Date: 20170218

ACTIVE INGREDIENTS: ALCOHOL 63 mL/100 mL
INACTIVE INGREDIENTS: WATER; GLYCERIN; PROPYLENE GLYCOL; CARBOMER INTERPOLYMER TYPE A (55000 CPS); AMINOMETHYLPROPANOL; DENATONIUM BENZOATE

Active Ingredient:
Ethyl Alcohol 63%

Purpose:
Antiseptic

Warnings:
For external use only. Flammable, keep away from fire, flame and direct sunlight.

STOP USE

Stop using this product and consult a doctor If irritation or redness develops.Stop using this product and consult a doctor If irritation or redness develops.

Directions

- Rub dime sized amount between hands until dry.
- For use by children under 6 years, adult supervision is required.

INACTIVE INGREDIENT

Water, Propylene Glycol, Carbomer, Aminomethyl Propanol, Glycerin, Denotonium Benzoate

INDICATIONS AND USAGE

Uses To help reduce bacteria on hands.

When using this product Avoid contact with eyes and lips. If contact occurs, rinse with water.

Keep out of reach of children. If swallowed, get medical help or contact a poison control center immediately.